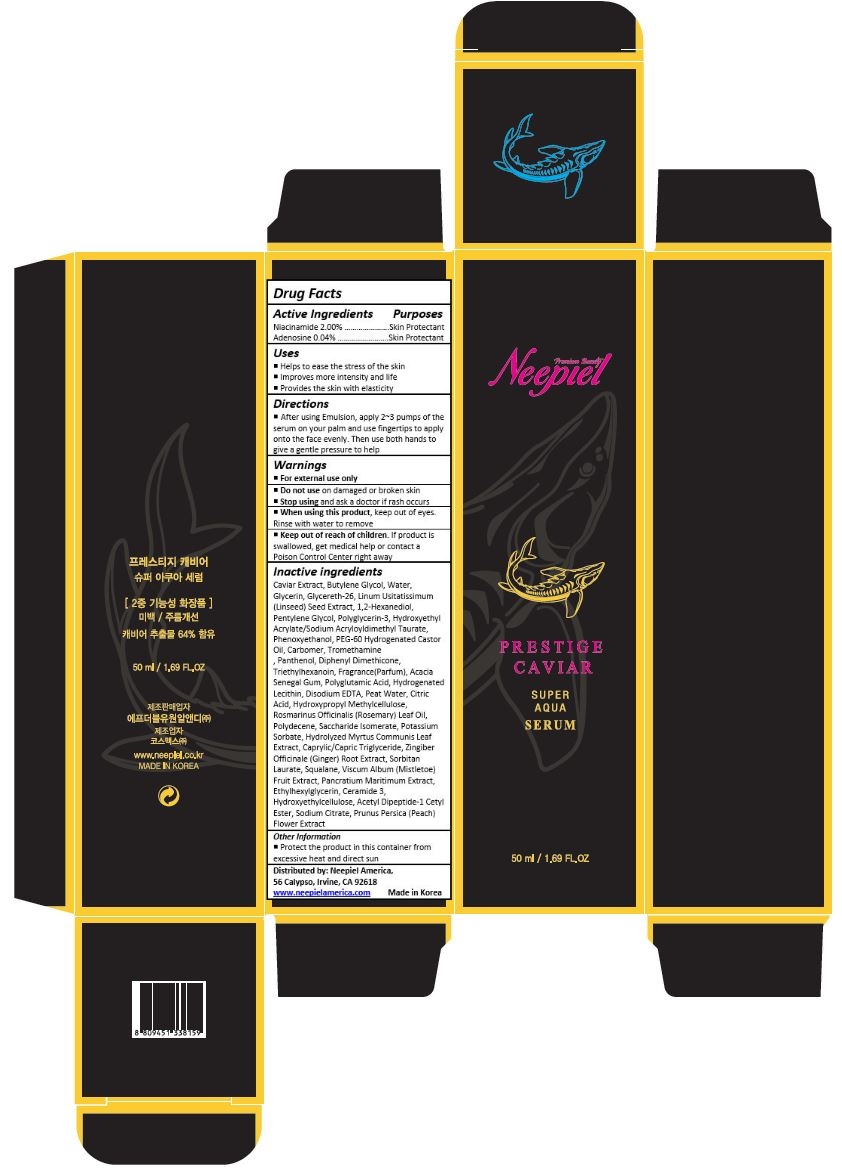 DRUG LABEL: Prestige Caviar Super Aqua Serum
NDC: 70519-005 | Form: CREAM
Manufacturer: FW1 R&D_Branch
Category: otc | Type: HUMAN OTC DRUG LABEL
Date: 20170627

ACTIVE INGREDIENTS: NIACINAMIDE 1 mg/50 mL; ADENOSINE 0.02 mg/50 mL
INACTIVE INGREDIENTS: CAVIAR, UNSPECIFIED; BUTYLENE GLYCOL; WATER; GLYCERIN; GLYCERETH-26; FLAX SEED; 1,2-HEXANEDIOL; PENTYLENE GLYCOL; POLYGLYCERIN-3; HYDROXYETHYL ACRYLATE/SODIUM ACRYLOYLDIMETHYL TAURATE COPOLYMER (100000 MPA.S AT 1.5%); PHENOXYETHANOL; PEG-60 HYDROGENATED CASTOR OIL; CARBOXYPOLYMETHYLENE; TROMETHAMINE; PANTHENOL; DIPHENYL DIMETHICONE (400 CST); TRIETHYLHEXANOIN; ACACIA; HYDROGENATED SOYBEAN LECITHIN; EDETATE DISODIUM; CITRIC ACID MONOHYDRATE; HYPROMELLOSES; ROSEMARY OIL; HYDROGENATED DIDECENE; SACCHARIDE ISOMERATE; POTASSIUM SORBATE; MYRTUS COMMUNIS LEAF; MEDIUM-CHAIN TRIGLYCERIDES; GINGER; SORBITAN MONOLAURATE; SQUALANE; VISCUM ALBUM FRUIT; ETHYLHEXYLGLYCERIN; CERAMIDE NP; HYDROXYETHYL CELLULOSE (100 MPA.S AT 2%); ACETYL TYROSYLARGININE CETYL ESTER; SODIUM CITRATE, UNSPECIFIED FORM; PRUNUS PERSICA FLOWER

Drug Facts

ACTIVE INGREDIENT

Niacinamide 2.00%
Adenosine 0.04%

PURPOSE

Skin Protectant

INDICATIONS AND USAGE

To provide hydration and promote attractiveness to skin

DOSAGE AND ADMINISTRATION

Apply gently over clean, dry skin or/and desired area 1 to 2 times daily

For morning and evening use

WARNINGS

For external use only.
Do not use on damaged or broken skin.
When using this product, keep out of eyes. Rinse with water to remove
Stop using and ask a doctor if rash occurs.

Keep out of reach of children.

If product is swallowed, get medical help or contact a Poison Control Center right away.

INACTIVE INGREDIENT

Caviar Extract, Butylene Glycol, Water, Glycerin, Glycereth-26, Linum Usitatissimum (Linseed) Seed Extract, 1,2-Hexanediol, Pentylene Glycol, Polyglycerin-3, Hydroxyethyl Acrylate/Sodium Acryloyldimethyl Taurate, Phenoxyethanol, PEG-60 Hydrogenated Castor Oil, Carbomer, Tromethamine
, Panthenol, Diphenyl Dimethicone, Triethylhexanoin, Fragrance(Parfum), Acacia Senegal Gum, Polyglutamic Acid, Hydrogenated Lecithin, Disodium EDTA, Peat Water, Citric Acid, Hydroxypropyl Methylcellulose, Rosmarinus Officinalis (Rosemary) Leaf Oil, Polydecene, Saccharide Isomerate, Potassium Sorbate, Hydrolyzed Myrtus Communis Leaf Extract, Caprylic/Capric Triglyceride, Zingiber Officinale (Ginger) Root Extract, Sorbitan Laurate, Squalane, Viscum Album (Mistletoe) Fruit Extract, Pancratium Maritimum Extract, Ethylhexylglycerin, Ceramide 3, Hydroxyethylcellulose, Acetyl Dipeptide-1 Cetyl Ester, Sodium Citrate, Prunus Persica (Peach) Flower Extract